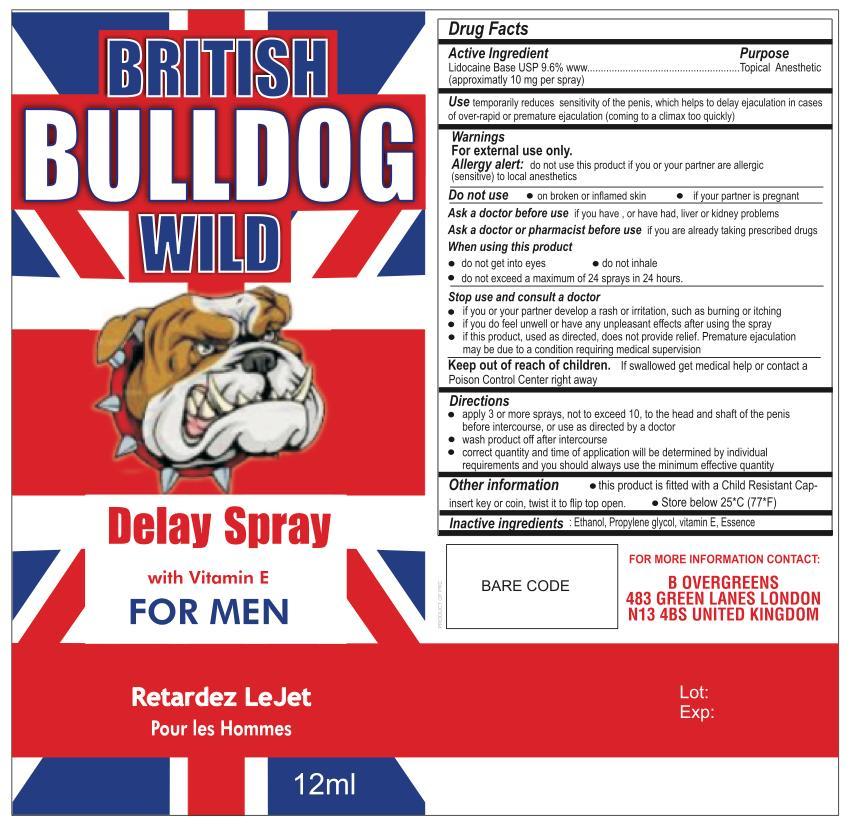 DRUG LABEL: Tiger delayspray
NDC: 59240-006 | Form: SPRAY
Manufacturer: Magverz INC
Category: otc | Type: HUMAN OTC DRUG LABEL
Date: 20170103

ACTIVE INGREDIENTS: LIDOCAINE 10 mg/100 mL
INACTIVE INGREDIENTS: ISOPROPYL MYRISTATE; STEARIC ACID; .ALPHA.-TOCOPHEROL

British Bull Dog

ACTIVE INGREDIENT

Lidocaine HCI 10 % ... External Anesthetic

Purpose

External Anesthetic

Keep out of Reach of Children

WARNINGS: Keep out of reach of children.

For External use only

Indication and Usage

temporarily reduces sensitivity of the penis, which helps to delay ejaculation in cases of over-rapid or premature ejaculation (coming to a climax too quickly)

Inactive Ingredients

Ethanol,Propyelene glycol, Vitamin E and Essence

Warning

Allergy alert: do not use this product if you or your partner are allergic (sensitive) to local Anesthetics.

Do not use - on broken or inflamed skin -if your partner is pregnant

Ask a doctor before use if you have, or ever had, liver or kidney problems

Ask a doctor or pharmacist before use if you are already taking prescribed drugs

when using this product

- do not get into eyes

- do not inhale

- do not exceed 24 sprays in 24 hours

Dosage and Administration

-apply 3 or more sprays, not to exceed 10, to the head and shaft of the penis before intercourse, or as directed by a doctor

-wash product after intercourse

-correct quantity and time of application will be determined by individual requirements and you should always use the minimum effective quantity